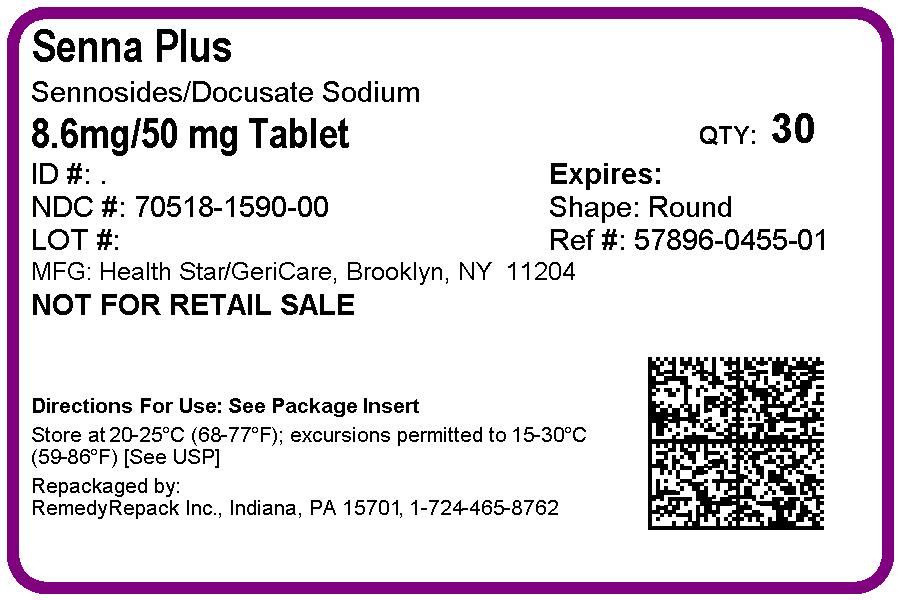 DRUG LABEL: Senna Plus
NDC: 70518-1590 | Form: TABLET
Manufacturer: REMEDYREPACK INC.
Category: otc | Type: HUMAN OTC DRUG LABEL
Date: 20191009

ACTIVE INGREDIENTS: SENNOSIDES 8.6 mg/1 1; DOCUSATE SODIUM 50 mg/1 1
INACTIVE INGREDIENTS: CELLULOSE, MICROCRYSTALLINE; CROSCARMELLOSE SODIUM; CALCIUM PHOSPHATE, DIBASIC, ANHYDROUS; MAGNESIUM SILICATE; MAGNESIUM STEARATE; MINERAL OIL; POLYETHYLENE GLYCOL, UNSPECIFIED; HYPROMELLOSES; FD&C YELLOW NO. 5; FD&C YELLOW NO. 6; SODIUM BENZOATE; SODIUM LAURYL SULFATE; STARCH, CORN; STEARIC ACID; TITANIUM DIOXIDE; TRIACETIN

Active ingredient (in each tablet)

Docusate Sodium 50 mg
Sennosides 8.6 mg

Purpose

Stool softener

Laxative

Uses

- relieves occasional constipation (irregularity)

- generally produces bowel movement in 6 to 12 hours

Warnings

Do not use for more than 1 week unless directed by a doctor

Ask a doctor before use if you -have abdominal pain, nausea or vomiting -are taking mineral oil -have noticed a sudden change in bowel habits that lasts over 2 weeks

Stop use and ask a doctor if -you have no bowel movement within 12 hours -you have rectal bleeding. these could signs of a serious condition.

if pregnant or breast-feeding, ask a health professional before use.

Keep out of reach of children. In case of overdose, get medical help or contact a Poison Control Center right away.

Directions

• do not exceed 8 tablets in 24 hours

Age | Starting Dose | Maximum Dose
adults and children 12 years of age and older | 2 tablets once a day preferably at bedtime; increase as needed, or as directed by a doctor | 4 tablets in the morning and 4 tablets at bedtime
children under 12 years | ask a doctor

Other information

• each tablet contains: calcium 7 mg

• store at room temperature

Inactive ingredients

cellulose, croscarmellose sodium, dicalcium phosphate, FD and C yellow no. 5 (tartrazine), FD and C yellow no. 6, hypromellose, magnesium silicate, magnesium stearate, mineral oil, PEG, sodium benzoate, sodium lauryl sulfate, starch, stearic acid, titanium dioxide, triacetin

PACKAGE LABEL

DRUG: Senna Plus

GENERIC: Sennosides and Docusate Sodium

DOSAGE: TABLET

ADMINSTRATION: ORAL

NDC: 70518-1590-0

COLOR: yellow

SHAPE: ROUND

SCORE: No score

SIZE: 10 mm

IMPRINT: CPC490

PACKAGING: 30 in 1 BLISTER PACK

ACTIVE INGREDIENT(S):

- DOCUSATE SODIUM 50mg in 1
- SENNOSIDES 8.6mg in 1

INACTIVE INGREDIENT(S):

- CELLULOSE, MICROCRYSTALLINE
- SODIUM BENZOATE
- FD&C YELLOW NO. 6
- SODIUM LAURYL SULFATE
- FD&C YELLOW NO. 5
- TITANIUM DIOXIDE
- STARCH, CORN
- STEARIC ACID
- CALCIUM PHOSPHATE, DIBASIC, ANHYDROUS
- CROSCARMELLOSE SODIUM
- HYPROMELLOSES
- MAGNESIUM SILICATE
- MAGNESIUM STEARATE
- POLYETHYLENE GLYCOLS
- MINERAL OIL
- TRIACETIN